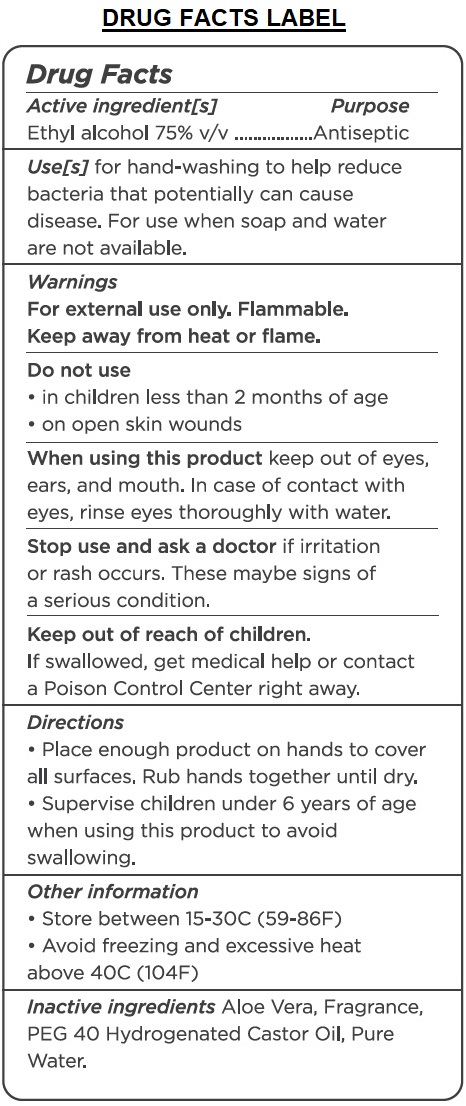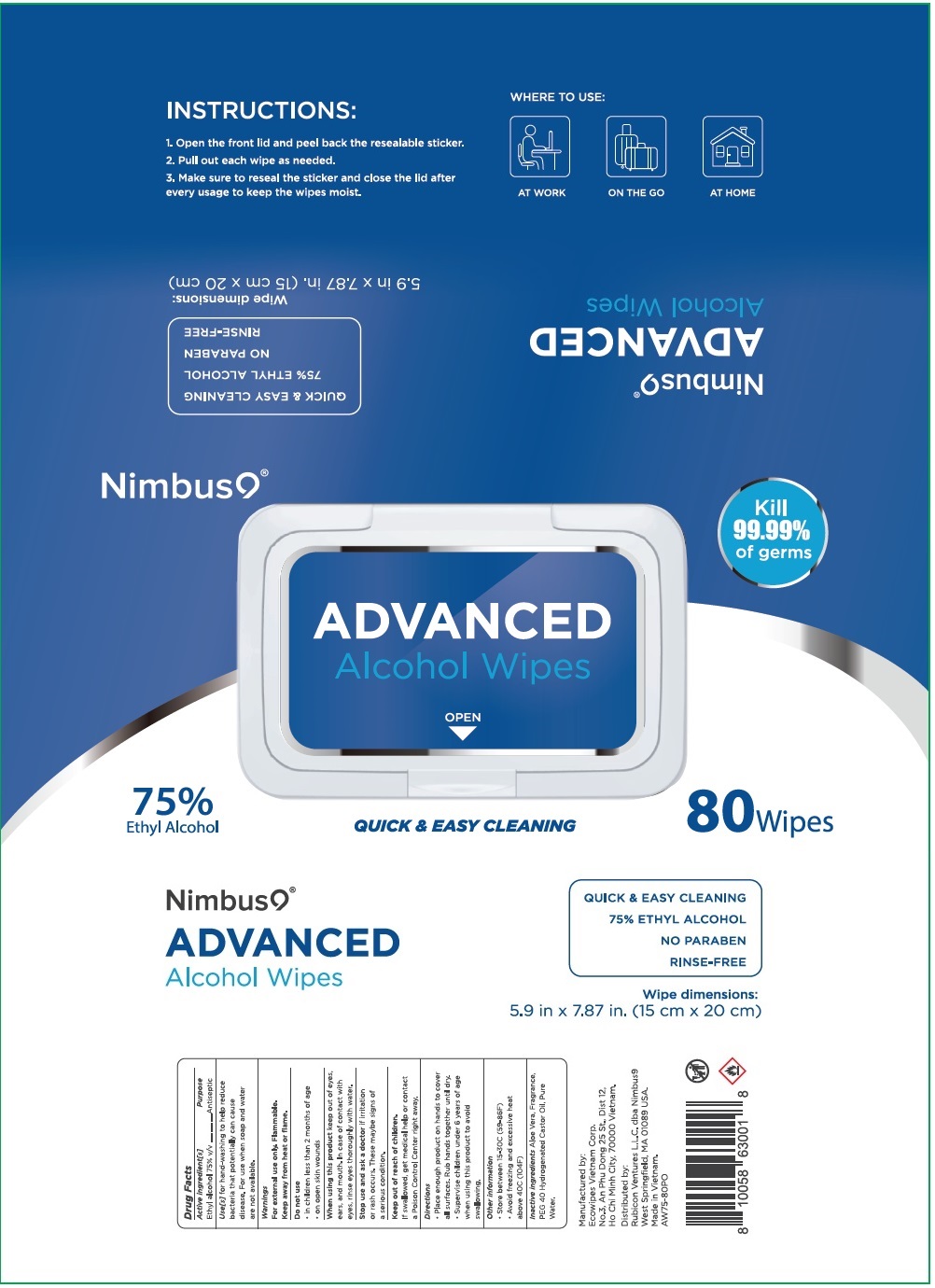 DRUG LABEL: ADVANCED ALCOHOL WIPES
NDC: 78898-375 | Form: CLOTH
Manufacturer: Eco Wipes Vietnam Corporation
Category: otc | Type: HUMAN OTC DRUG LABEL
Date: 20200804

ACTIVE INGREDIENTS: ALCOHOL 75 mL/100 mL
INACTIVE INGREDIENTS: ALOE VERA LEAF; POLYOXYL 40 HYDROGENATED CASTOR OIL; WATER

Nimbus9® ADVANCED Alcohol Wipes

Active ingredient[s]

Ethyl alcohol 75% v/v

Purpose

Antiseptic

INDICATIONS AND USAGE

Use[s] for hand-washing to help reduce bacteria that potentially can cause disease. For use when soap and water are not available.

Warnings

For external use only. Flammable.

Keep away from heat or flame.

Do not use

• in children less than 2 months of age

• on open skin wounds

When using this product keep out of eyes, ears, and mouth. In case of contact with eyes, rinse thoroughly with water.

Stop use and ask a doctor if irritation or rash occurs. These may be signs of a serious condition.

Keep out of reach of children.

If swallowed, get medical hep or contact a Poison Control Center right away.

Directions

• Place enough product on hands to cover all surfaces. Rub hands together until dry.

• Supervise children under 6 years of age when using this product to avoid swallowing.

Other information

• Store between 15-30C (59-86F)

• Avoid freezing and excessive heat above 40C (104F)

INACTIVE INGREDIENT

Inactive ingredients Aloe Vera, Fragrance, PEG 40 Hydrogenated Castor Oil, Pure Water.

Kill 99.99% of germs

QUICK & EASY CLEANING

75% ETHYL ALCOHOL

NO PARABEN

RINSE-FREE

INSTRUCTIONS:

1.Open the front lid and peel back the resealable sticker.

2. Pull out each wipe as needed.

3.Make sure to reseal the sticker and close the lid after every usage to keep the wipes moist.

WHERE TO USE:

AT WORK

ON THE GO

AT HOME

Manufactured by:

Ecowipes Vietnam Corp.

No.3, An Phu Dong 25 St., Dist 12,

Ho Chi Minh City, 70000 Vitenam.

Distributed by:

Rubicon Ventures L.L.C. dba Nimbus9

West Springfield, MA 01089 USA.

Made in Vietnam.

AW75-80PO